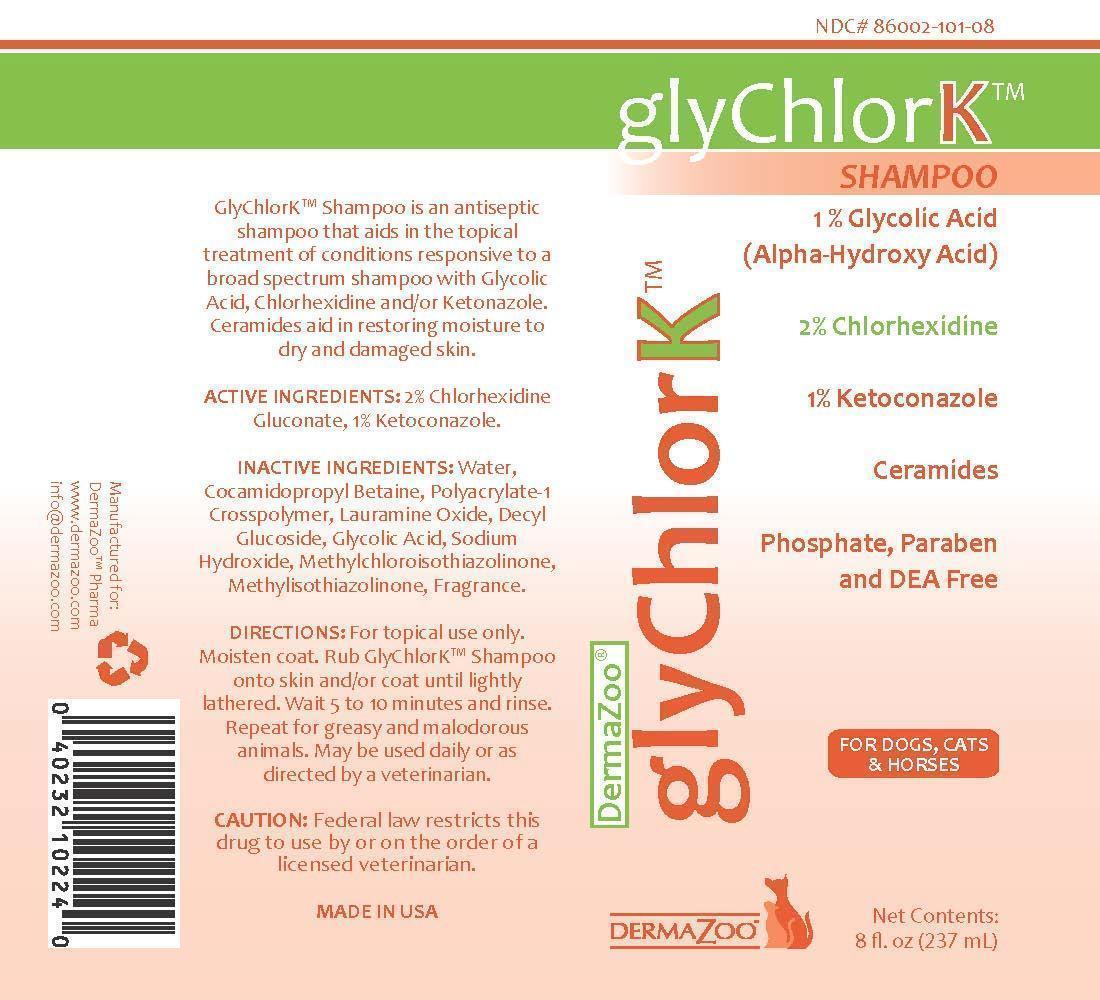 DRUG LABEL: GlyChlorK
NDC: 86002-101 | Form: SHAMPOO
Manufacturer: DermaZoo, LLC
Category: animal | Type: PRESCRIPTION ANIMAL DRUG LABEL
Date: 20240821

ACTIVE INGREDIENTS: CHLORHEXIDINE GLUCONATE 2 g/1000 mL; KETOCONAZOLE 1 g/1000 mL
INACTIVE INGREDIENTS: WATER; COCAMIDOPROPYL BETAINE; POLYACRYLIC ACID (8000 MW); LAURAMINE OXIDE; DECYL GLUCOSIDE; GLYCOLIC ACID; SODIUM HYDROXIDE; METHYLCHLOROISOTHIAZOLINONE; METHYLISOTHIAZOLINONE

INDICATIONS AND USAGE

GlyChlorK™ Shampoo is an antiseptic shampoo that aids in the topical treatment of conditions responsive to a broad spectrum shampoo with Glycolic Acid, Chlorhexidine and/or Ketonazole. Ceramides aid in restoring moisture to dry and damaged skin.

DIRECTIONS: For topical use only. Moisten coat. Rub GlyChlorK™ Shampoo onto skin and/or coat until lightly lathered. Wait 5 to 10 minutes and rinse. Repeat for greasy and malodorous animals. May be used daily or as directed by a veterinarian.

WARNINGS AND PRECAUTIONS

CAUTION: Federal law restricts this drug to use by or on the order of a licensed veterinarian.

DESCRIPTION SECTION

ACTIVE INGREDIENTS: 2% Chlorhexidine Gluconate, 1% Ketoconazole.

INACTIVE INGREDIENTS: Water, Cocamidopropyl Betaine, Polyacrylate-1, Crosspolymer, Lauramine Oxide, Decyl Glucoside, Glycolic Acid, Sodium Hydroxide, Methylchloroisothiazolinone, Methylisothiazolinone, Fragrance.

GlyChlorK™ Shampoo

1% Glycolic Acid (Alpha-Hydroxy Acid)

2% Chlorhexidine

1% Ketoconazole

Ceramides

Phosphate, Paraben, and DEA Free

For Dogs, Cats, and Horses

Net contents 8 fl. oz. (237 mL)

Made in USA

Manufactured for Dermazoo™ Pharma, www.dermazoo.com, info@dermazoo.com